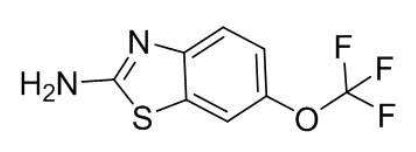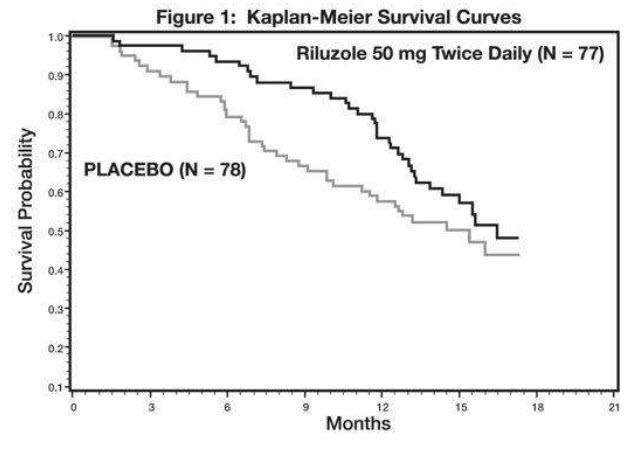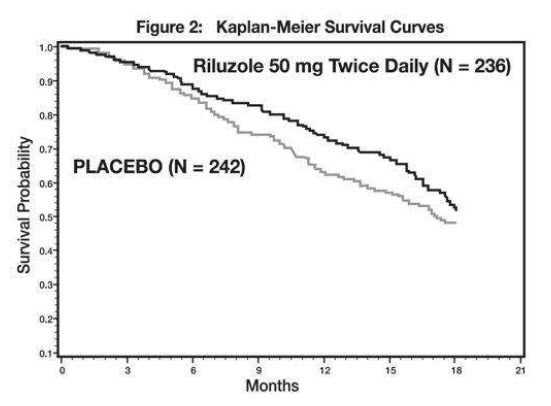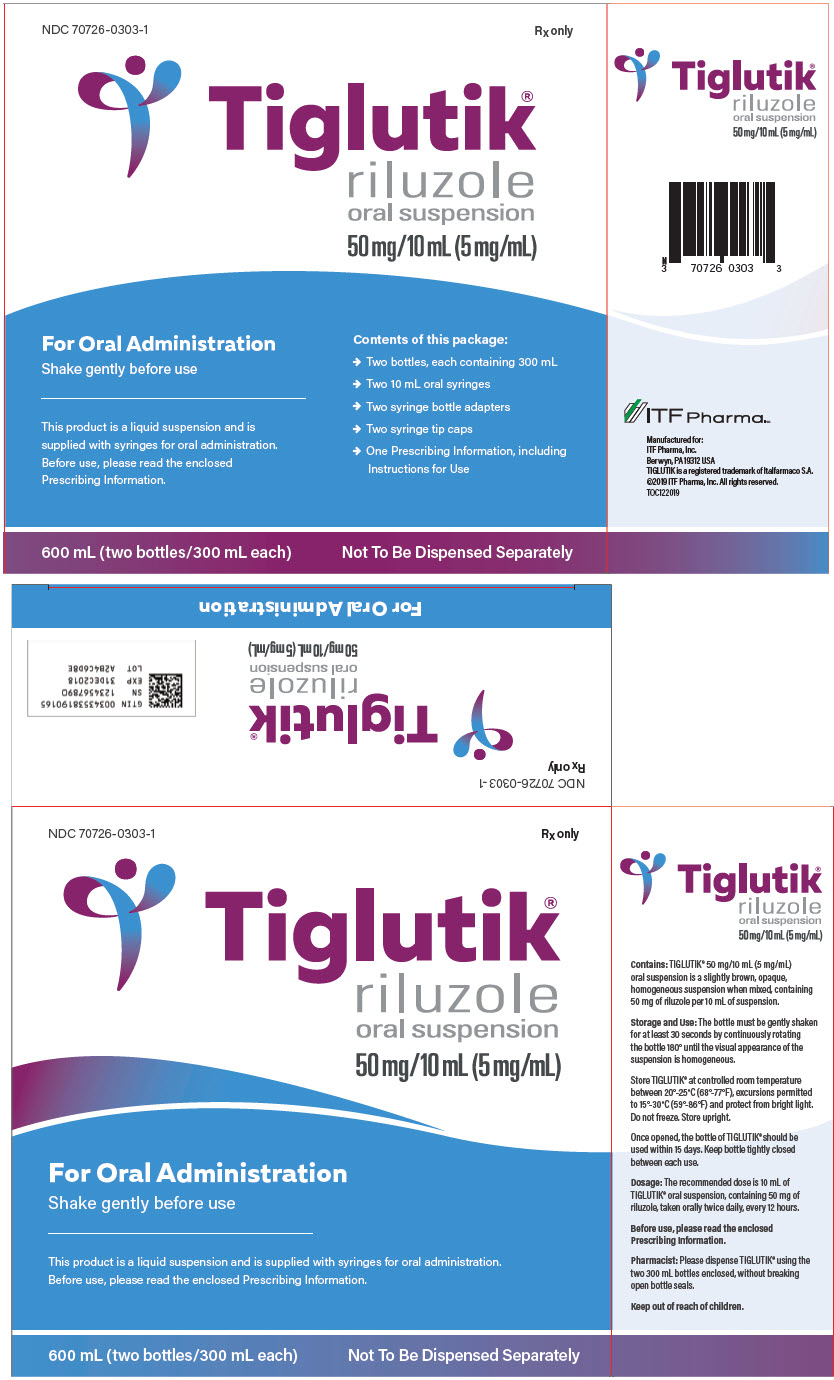 DRUG LABEL: TIGLUTIK
NDC: 70726-0303 | Form: LIQUID
Manufacturer: EDW PHARMA, INC
Category: prescription | Type: HUMAN PRESCRIPTION DRUG LABEL
Date: 20251231

ACTIVE INGREDIENTS: RILUZOLE 50 mg/10 mL
INACTIVE INGREDIENTS: SORBITOL; POLYOXYL 20 CETOSTEARYL ETHER; MAGNESIUM ALUMINUM SILICATE; DIMETHICONE; WATER; SACCHARIN SODIUM; SILICON DIOXIDE; SODIUM LAURYL SULFATE; XANTHAN GUM

HIGHLIGHTS OF PRESCRIBING INFORMATION

These highlights do not include all the information needed to use TIGLUTIK® safely and effectively. See full prescribing information for TIGLUTIK.
TIGLUTIK (riluzole) oral suspension
Initial U.S. Approval: 1995

RECENT MAJOR CHANGES

Dosage and Administration (2.1, 2.3) | 12/2019

1 INDICATIONS AND USAGE

TIGLUTIK is indicated for the treatment of amyotrophic lateral sclerosis (ALS) (1)

2 DOSAGE AND ADMINISTRATION

- Recommended dosage: 50 mg (10 mL), twice daily, taken orally or via percutaneous endoscopic gastrostomy tubes (PEG-tubes), every 12 hours (2.1)
- Measure serum aminotransferases before and during treatment (2.2, 5.1)
- Take at least 1 hour before or 2 hours after a meal (2.3)

3 DOSAGE FORMS AND STRENGTHS

Oral suspension: 50 mg/10 mL (5 mg/mL) in 300 mL multiple-dose bottle (3)

4 CONTRAINDICATIONS

Patients with a history of severe hypersensitivity reactions to riluzole or to any of its components (4)

5 WARNINGS AND PRECAUTIONS

- Hepatic injury: Use of TIGLUTIK is not recommended in patients with baseline elevations of serum aminotransferases greater than 5 times the upper limit of normal; discontinue TIGLUTIK if there is evidence of liver dysfunction (5.1)
- Neutropenia: Advise patients to report any febrile illness (5.2)
- Interstitial lung disease: Discontinue TIGLUTIK if interstitial lung disease develops (5.3)

6 ADVERSE REACTIONS

Most common adverse reactions (incidence greater than or equal to 5% and greater than placebo) were oral hypoesthesia, asthenia, nausea, decreased lung function, hypertension, and abdominal pain (6.1)

To report SUSPECTED ADVERSE REACTIONS, contact ITF Pharma Inc. at 1-800-664-1490 or FDA at 1-800-FDA-1088 or www.fda.gov/medwatch.

7 DRUG INTERACTIONS

- Strong to moderate CYP1A2 inhibitors: Co-administration may increase TIGLUTIK-associated adverse reactions (7.1)
- Strong to moderate CYP1A2 inducers: Co-administration may result in decreased efficacy (7.2)
- Hepatotoxic drugs: TIGLUTIK-treated patients that take other hepatotoxic drugs may be at increased risk for hepatotoxicity (7.3)

8 USE IN SPECIFIC POPULATIONS

- Pregnancy: Based on animal data, may cause fetal harm (8.1)

FULL PRESCRIBING INFORMATION

1 INDICATIONS AND USAGE

TIGLUTIK is indicated for the treatment of amyotrophic lateral sclerosis (ALS).

2 DOSAGE AND ADMINISTRATION

2.1 Dosage Information

The recommended dosage for TIGLUTIK is 50 mg (10 mL) taken orally or via Percutaneous Endoscopic Gastrostomy tubes (PEG-tubes) twice daily, every 12 hours. TIGLUTIK should be taken at least 1 hour before or 2 hours after a meal [see Clinical Pharmacology (12.3)].

2.2 Monitoring to Assess Safety

Measure serum aminotransferases before and during treatment with TIGLUTIK [see Warnings and Precautions (5.1)].

2.3 Important Administration Instructions

Gently shake the TIGLUTIK bottle for at least 30 seconds before administration.Gently shake the TIGLUTIK bottle for at least 30 seconds before administration.

TIGLUTIK can be administered by mouth or via percutaneous endoscopic gastrostomy tubes (PEG-tubes). Both silicone and polyurethane PEG tubes can be used.

See the Instructions for Use for further administration details.See the Instructions for Use for further administration details.

3 DOSAGE FORMS AND STRENGTHS

Oral suspension: 50 mg/10 mL (5 mg/mL) slightly brown, opaque, homogeneous suspension in a 300-mL multiple-dose amber bottle.

4 CONTRAINDICATIONS

TIGLUTIK is contraindicated in patients with a history of severe hypersensitivity reactions to riluzole or to any of its components (anaphylaxis has occurred) [see Adverse Reactions (6.1)].

5 WARNINGS AND PRECAUTIONS

5.1 Hepatic Injury

TIGLUTIK can cause liver injury. Cases of drug-induced liver injury, some of which were fatal, have been reported in patients taking riluzole. Asymptomatic elevations of hepatic transaminases have also been reported, and in some patients have recurred upon re-challenge with riluzole.

In clinical studies, the incidence of elevations in hepatic transaminases was greater in riluzole-treated patients than placebo-treated patients. The incidence of elevations of ALT above 5 times the upper limit of normal (ULN) was 2% in riluzole-treated patients. Maximum increases in ALT occurred within 3 months after starting riluzole. About 50% and 8% of riluzole-treated patients in pooled controlled efficacy studies (Studies 1 and 2) had at least one elevated ALT level above ULN and above 3 times ULN, respectively [see Clinical Studies (14)].

Monitor patients for signs and symptoms of hepatic injury, every month for the first 3 months of treatment, and periodically thereafter. The use of TIGLUTIK is not recommended if patients develop hepatic transaminases levels greater than 5 times the ULN. Discontinue TIGLUTIK if there is evidence of liver dysfunction (e.g., elevated bilirubin). Concomitant use with other hepatotoxic drugs may increase the risk for hepatotoxicity [see Drug Interactions (7.3)] .

5.2 Neutropenia

TIGLUTIK can cause neutropenia. Cases of severe neutropenia (absolute neutrophil count less than 500 per mm^3) within the first 2 months of riluzole treatment have been reported. Advise patients to report febrile illnesses.

5.3 Interstitial Lung Disease

TIGLUTIK can cause interstitial lung disease, including hypersensitivity pneumonitis. Discontinue TIGLUTIK immediately if interstitial lung disease develops.

6 ADVERSE REACTIONS

The following adverse reactions are described below and elsewhere in the labeling:

- Hepatic Injury [see Warnings and Precautions (5.1)]
- Neutropenia [see Warnings and Precautions (5.2)]
- Interstitial Lung Disease [see Warnings and Precautions (5.3)]

6.1 Clinical Trials Experience

Because clinical trials are conducted under widely varying conditions, adverse reaction rates observed in the clinical trials of a drug cannot be directly compared to rates in the clinical trials of another drug and may not reflect the rates observed in practice.

Adverse Reactions in Controlled Clinical Trials of Riluzole Tablets

In the placebo-controlled clinical trials in patients with ALS (Study 1 and 2), a total of 313 patients received riluzole 50 mg twice daily [see Clinical Studies (14)]. The most common adverse reactions in riluzole-treated patients (in at least 5% of patients and more frequently than on placebo) were asthenia, nausea, decreased lung function, hypertension, and abdominal pain. The most common adverse reactions leading to discontinuation in the riluzole group were nausea, abdominal pain, constipation, and elevated ALT.

There was no difference in the rate of adverse reactions leading to discontinuation between females and males. However, the incidence of dizziness was higher in females (11%) than in males (4%). The adverse reaction profile was similar in older and younger patients. There are insufficient data to assess racial differences in the adverse reaction profile.

Table 1 lists adverse reactions that occurred in at least 2% of riluzole-treated patients (50 mg twice daily) in pooled Study 1 and 2, and at a higher rate than on placebo.

Table 1. Adverse Reactions in Pooled Placebo-Controlled Trials (Studies 1 and 2) in Patients with ALS
Adverse Reaction | Riluzole Tablets 50 mg twice daily (N=313) % | Placebo (N=320) %
Asthenia | 19 | 12
Nausea | 16 | 11
Decreased lung function | 10 | 9
Hypertension | 5 | 4
Abdominal pain | 5 | 4
Vomiting | 4 | 2
Arthralgia | 4 | 3
Dizziness | 4 | 3
Dry mouth | 4 | 3
Insomnia | 4 | 3
Pruritus | 4 | 3
Tachycardia | 3 | 1
Flatulence | 3 | 2
Increased cough | 3 | 2
Peripheral edema | 3 | 2
Urinary Tract Infection | 3 | 2
Circumoral paresthesia | 2 | 0
Somnolence | 2 | 1
Vertigo | 2 | 1
Eczema | 2 | 1

Additional Adverse Reactions with TIGLUTIK

In an open-label pharmacokinetic study in healthy subjects (n=36), oral hypoesthesia was observed in 29% of subjects taking TIGLUTIK, compared to 6% in patients taking riluzole tablets, under fasting conditions.

6.2 Postmarketing Experience

The following adverse reactions have been identified during post-approval use of riluzole. Because these reactions are reported voluntarily from a population of uncertain size, it is not always possible to reliably estimate their frequency or establish a causal relationship to drug exposure.

- Acute hepatitis and icteric toxic hepatitis [see Warnings and Precautions (5.1)]
- Renal tubular impairment
- Pancreatitis

7 DRUG INTERACTIONS

7.1 Agents that may Increase Riluzole Blood Concentrations

CYP1A2 Inhibitors

Co-administration of riluzole (a CYP1A substrate) with CYP1A2 inhibitors was not evaluated in a clinical trial; however, in vitro findings suggest an increase in riluzole exposure is likely. The concomitant use of strong or moderate CYP1A2 inhibitors (e.g., ciprofloxacin, enoxacin, fluvoxamine, methoxsalen, mexiletine, oral contraceptives, thiabendazole, vemurafenib, zileuton) with TIGLUTIK may increase the risk of TIGLUTIK - associated adverse reactions [see Clinical Pharmacology (12.3)].

7.2 Agents that may Decrease Riluzole Plasma Concentrations

CYP1A2 Inducers

Co-administration of riluzole (a CYP1A substrate) with CYP1A2 inducers was not evaluated in a clinical trial; however, in vitro findings suggest a decrease in riluzole exposure is likely. Lower exposures may result in decreased efficacy [see Clinical Pharmacology (12.3)] .

7.3 Hepatotoxic Drugs

Clinical trials in ALS patients excluded patients on concomitant medications which were potentially hepatotoxic (e.g., allopurinol, methyldopa, sulfasalazine). TIGLUTIK-treated patients who take other hepatotoxic drugs may be at an increased risk for hepatotoxicity [see Warnings and Precautions (5.1)].

8 USE IN SPECIFIC POPULATIONS

8.1 Pregnancy

Risk Summary

There are no studies of riluzole in pregnant women, and case reports have been inadequate to inform the drug-associated risk. The background risk for major birth defects and miscarriage in patients with amyotrophic lateral sclerosis is unknown. In the U.S. general population, the background risk of major birth defects and miscarriage in clinically recognized pregnancies is 2-4% and 15-20%, respectively.

In studies in which riluzole was administered orally to pregnant animals, developmental toxicity (decreased embryofetal/offspring viability, growth, and functional development) was observed at clinically relevant doses [see Data] . Based on these results, women should be advised of a possible risk to the fetus associated with use of TIGLUTIK during pregnancy.

Data

Animal Data

Oral administration of riluzole (3, 9, or 27 mg/kg/day) to pregnant rats during the period of organogenesis resulted in decreases in fetal growth (body weight and length) at the high dose. The mid dose, a no-effect dose for embryofetal developmental toxicity, is approximately equal to the recommended human daily dose (RHDD, 100 mg) on a mg/m2 basis. When riluzole was administered orally (3, 10, or 60 mg/kg/day) to pregnant rabbits during the period of organogenesis, embryofetal mortality was increased at the high dose and fetal body weight was decreased and morphological variations increased at all but the lowest dose tested. The no-effect dose (3 mg/kg/day) for embryofetal developmental toxicity is less than the RHDD on a mg/m2 basis. Maternal toxicity was observed at the highest dose tested in rat and rabbit.

When riluzole was orally administered (3, 8, or 15 mg/kg/day) to male and female rats prior to and during mating and to female rats throughout gestation and lactation, increased embryofetal mortality and decreased postnatal offspring viability, growth, and functional development were observed at the high dose. The mid dose, a no-effect dose for pre- and postnatal developmental toxicity, is approximately equal to the RHDD on a mg/m2 basis.

8.2 Lactation

Risk Summary

There are no data on the presence of riluzole in human milk, the effects on the breastfed infant, or the effects on milk production. Riluzole or its metabolites have been detected in milk of lactating rat. The developmental and health benefits of breastfeeding should be considered along with the mother's clinical need for TIGLUTIK and any potential adverse effects on the breastfed infant from TIGLUTIK or from the underlying maternal condition.

8.3 Females and Males of Reproductive Potential

In rats, oral administration of riluzole resulted in decreased fertility indices and increases in embryolethality [see Nonclinical Toxicology (13.1)].

8.4 Pediatric Use

Safety and effectiveness in pediatric patients have not been established.

8.5 Geriatric Use

In clinical studies of riluzole, 30% of patients were 65 years and over. No overall differences in safety or effectiveness were observed between these patients and younger patients, and other reported clinical experience has not identified differences in responses between the elderly and younger patients, but greater sensitivity of some older individuals cannot be ruled out.

8.6 Hepatic Impairment

Patients with mild [Child-Pugh's (CP) score A] or moderate (CP score B) hepatic impairment had increases in AUC, compared to patients with normal hepatic function. Thus, patients with mild or moderate hepatic impairment may be at increased risk of adverse reactions. The impact of severe hepatic impairment on riluzole exposure is unknown.

Use of TIGLUTIK is not recommended in patients with baseline elevations of serum aminotransferases greater than 5 times upper limit of normal or evidence of liver dysfunction (e.g., elevated bilirubin) [see Clinical Pharmacology (12.3)].

8.7 Japanese Patients

Japanese patients are more likely to have higher riluzole concentrations. Consequently, the risk of adverse reactions may be greater in Japanese patients [see Clinical Pharmacology (12.3)].

10 OVERDOSAGE

Reported symptoms of overdose following ingestion of riluzole ranging from 1.5 to 3 grams (30 to 60 times the recommended dose) included acute toxic encephalopathy, coma, drowsiness, memory loss, and methemoglobinemia.

No specific antidote for the treatment of TIGLUTIK overdose is available. For current information on the management of poisoning or overdosage, contact a certified poison control center.

11 DESCRIPTION

Riluzole is a member of the benzothiazole class. The chemical designation for riluzole is 2-amino-6-(trifluoromethoxy)benzothiazole. Its molecular formula is C8H5F3N2OS, and its molecular weight is 234.2. The chemical structure is:

Riluzole is a white to slightly yellow powder that is very soluble in dimethylformamide, dimethylsulfoxide, and methanol; freely soluble in dichloromethane; sparingly soluble in 0.1 N HCl; and very slightly soluble in water and in 0.1 N NaOH.

TIGLUTIK (50 mg/10mL) oral suspension is a slightly brown, opaque, homogeneous suspension containing 50 mg of riluzole per 10 mL of suspension.

TIGLUTIK also contains the following inactive ingredients: magnesium aluminum silicate, noncrystallizing sorbitol solution, polyoxyl 20 cetostearyl ether, purified water, saccharin sodium, simethicone emulsion, sodium lauryl sulfate, and xanthan gum.

12 CLINICAL PHARMACOLOGY

12.1 Mechanism of Action

The mechanism by which riluzole exerts its therapeutic effects in patients with ALS is unknown.

12.2 Pharmacodynamics

The clinical pharmacodynamics of riluzole has not been determined in humans.

12.3 Pharmacokinetics

A pharmacokinetic study in healthy adult subjects who received riluzole suspension 50 mg under fasting conditions demonstrated similar pharmacokinetics following intragastric administration via feeding tubes and oral administration.

Table 2 displays the pharmacokinetic parameters of riluzole.

Table 2. Pharmacokinetics of Riluzole [Unless otherwise stated, information in this table is based on pharmacokinetic studies of riluzole tablets.]
Absorption
Bioavailability (oral) | Approximately 60%
Dose Proportionality | Linear over a dose range of 25 mg to 100 mg every 12 hours (1/2 to 2 times the recommended dosage)
Food effect [Information specific to TIGLUTIK] | AUC ↓ 9% and Cmax ↓ 55% (high fat meal)
Time to peak plasma concentration (median) | 0.8 hours
Distribution
Plasma Protein Binding | 96% (Mainly to albumin and lipoproteins)
Elimination
Elimination half-life | - 12 hours (CV=35%) - The high individual variability in the clearance of riluzole is potentially attributable to variability of CYP1A2. The clinical implications are not known.
Accumulation | Approximately 2-fold
Metabolism
Fraction metabolized (% dose) | At least 88%
Primary metabolic pathway(s) [in vitro] | - Oxidation: CYP1A2 - Direct and sequential glucoronidation: UGT-HP4
Active Metabolites | Some metabolites appear pharmacologically active in vitro, but the clinical implications are not known.
Excretion
Primary elimination pathways (% dose) | - Feces: 5% - Urine: 90% (2% unchanged riluzole)

Specific Populations

Hepatic Impairment

Compared with healthy volunteers, the AUC of riluzole was approximately 1.7-fold greater in patients with mild chronic hepatic impairment (CP score A), and approximately 3-fold greater in patients with moderate chronic hepatic impairment (CP score B). The pharmacokinetics of riluzole have not been studied in patients with severe hepatic impairment (CP score C) [see Use in Specific Populations (8.6)].

Race

The clearance of riluzole was 50% lower in male Japanese subjects than in Caucasian subjects, after normalizing for body weight [see Use in Specific Populations (8.7)].

Gender

The mean AUC of riluzole was approximately 45% higher in female patients than male patients.

Smokers

The clearance of riluzole in tobacco smokers was 20% greater than in nonsmokers. Geriatric Patients and Patients with Moderate to Severe Renal ImpairmentAge 65 years or older and moderate to severe renal impairment do not have a meaningful effect on the pharmacokinetics of riluzole. The pharmacokinetics of riluzole in patients undergoing hemodialysis are unknown.

Drug Interaction Studies

Drugs Highly Bound to Plasma Proteins

Riluzole and warfarin are highly bound to plasma proteins. In vitro, riluzole did not show any displacement of warfarin from plasma proteins. Riluzole binding to plasma proteins was unaffected by warfarin, digoxin, imipramine and quinine at high therapeutic concentrations in vitro.

13 NONCLINICAL TOXICOLOGY

13.1 Carcinogenesis, Mutagenesis, Impairment of Fertility

Carcinogenesis

Riluzole was not carcinogenic in mice or rats when administered for 2 years at daily oral doses up to 20 and 10 mg/kg/day, respectively, which are approximately equal to the recommended human daily dose (RHDD, 100 mg) on a mg/m2 basis.

Mutagenesis

Riluzole was negative in in vitro(bacterial reverse mutation (Ames), mouse lymphoma tk, chromosomal aberration assay in human lymphocytes), and in in vivo(rat cytogenetic and mouse micronucleus) assays.

N-hydroxyriluzole, the major active metabolite of riluzole, was positive for clastogenicity in the in vitro mouse lymphoma tk assay and in the in vitro micronucleus assay using the same mouse lymphoma cell line. N-hydroxyriluzole was negative in the HPRT gene mutation assay, the Ames assay (with and without rat or hamster S9), the in vitro chromosomal aberration assay in human lymphocytes, and the in vivo mouse micronucleus assay.

Impairment of Fertility

When riluzole (3, 8, or 15 mg/kg) was administered orally to male and female rats prior to and during mating and continuing in females throughout gestation and lactation, fertility indices were decreased and embryolethality was increased at the high dose. This dose was also associated with maternal toxicity. The mid dose, a no-effect dose for effects on fertility and early embryonic development, is approximately equal to the RHDD on a mg/m2 basis.

14 CLINICAL STUDIES

The efficacy of TIGLUTIK is based upon bioavailability studies comparing oral riluzole tablets to TIGLUTIK oral suspension [see Clinical Pharmacology (12.3)].

The efficacy of riluzole was demonstrated in two studies (Study 1 and 2) that evaluated 50 mg riluzole oral tablets twice daily in patients with amyotrophic lateral sclerosis (ALS). Both studies included patients with either familial or sporadic ALS, disease duration of less than 5 years, and baseline forced vital capacity greater than or equal to 60% of normal.

Study 1 was a randomized, double-blind, placebo-controlled clinical study that enrolled 155 patients with ALS. Patients were randomized to receive riluzole 50 mg twice daily (n=77) or placebo (n=78) and were followed for at least 13 months (up to a maximum duration of 18 months). The clinical outcome measure was time to tracheostomy or death.

The time to tracheostomy or death was longer for patients receiving riluzole compared to placebo. There was an early increase in survival in patients receiving riluzole compared to placebo. Figure 1 displays the survival curves for time to death or tracheostomy. The vertical axis represents the proportion of individuals alive without tracheostomy at various times following treatment initiation (horizontal axis). Although these survival curves were not statistically significantly different when evaluated by the analysis specified in the study protocol (Logrank test p=0.12), the difference was found to be significant by another appropriate analysis (Wilcoxon test p=0.05). As seen in Figure 1, the study showed an early increase in survival in patients given riluzole. Among the patients in whom the endpoint of tracheostomy or death was reached during the study, the difference in median survival between the riluzole 50 mg twice daily and placebo groups was approximately 90 days.

Figure 1. Time to Tracheostomy or Death in ALS Patients in Study 1 (Kaplan-Meier Curves)

Study 2 was a randomized, double-blind, placebo-controlled clinical study that enrolled 959 patients with ALS. Patients were randomized to riluzole 50 mg twice daily (n=236) or placebo (n=242) and were followed for at least 12 months (up to a maximum duration of 18 months). The clinical outcome measure was time to tracheostomy or death.

The time to tracheostomy or death was longer for patients receiving riluzole compared to placebo. Figure 2 displays the survival curves for time to death or tracheostomy for patients randomized to either riluzole 100 mg per day or placebo. Although these survival curves were not statistically significantly different when evaluated by the analysis specified in the study protocol (Logrank test p=0.076), the difference was found to be significant by another appropriate analysis (Wilcoxon test p=0.05). Not displayed in Figure 2 are the results of riluzole 50 mg per day (one-half of the recommended daily dose), which could not be statistically distinguished from placebo, or the results of riluzole 200 mg per day (two times the recommended daily dose), which were not distinguishable from the 100 mg per day results. Among the patients in whom the endpoint of tracheostomy or death was reached during the study, the difference in median survival between riluzole and placebo was approximately 60 days.

Although riluzole improved survival in both studies, measures of muscle strength and neurological function did not show a benefit.

Figure 2. Time to Tracheostomy or Death in ALS Patients in Study 2 (Kaplan-Meier Curves)

16 HOW SUPPLIED/STORAGE AND HANDLING

16.1 How Supplied

TIGLUTIK (50 mg/10 mL) oral suspension is supplied in amber glass bottles closed with child-resistant tamper evident screw caps. Each bottle contains 300 mL of oral suspension and is intended for multi-dose use, NDC 70726-0303-2.

TIGLUTIK is supplied in a carton, NDC 70726-0303-1, containing:

- Two bottles, each containing 300 mL oral suspension
- Two 10 mL oral syringes
- Two syringe bottle adapters
- Two syringe tip caps
- Prescribing Information, including Instructions for Use

16.2 Storage and Handling

Store at 20-25°C (68-77°F), excursions permitted to 15-30°C (59-86°F) [see USP Controlled Room Temperature], and protect from bright light. Do not freeze. Store upright.

Use within 15 days after initially opening of each bottle. Discard any unused TIGLUTIK remaining after 15 days of first opening of the bottle.

17 PATIENT COUNSELING INFORMATION

Advise the patient to read the FDA-approved patient labeling (Instructions for Use).

Administration Instructions

Instruct patients to discard any unused TIGLUTIK after 15 days of opening the bottle. If the patient requires administration of TIGLUTIK via PEG tube, refer the patient/caregiver to the Instructions for Use for steps on how to take/give TIGLUTIK.

Hepatic Injury

Advise patients that TIGLUTIK can cause liver injury, which can be fatal. Inform patients of the clinical signs or symptoms suggestive of hepatic dysfunction (e.g., unexplained nausea, vomiting, abdominal pain, fatigue, anorexia, or jaundice and/or dark urine) and to contact a healthcare provider promptly if these signs or symptoms occur [see Warnings and Precautions (5.1)].

Neutropenia

Advise patients that TIGLUTIK can cause neutropenia, and to report to their healthcare provider if they have a fever [see Warnings and Precautions (5.2)].

Interstitial Lung Disease

Advise patients that TIGLUTIK can cause interstitial lung disease, and to report to their healthcare provider if they have respiratory symptoms (e.g., dry cough and difficult or labored breathing) [see Warnings and Precautions (5.3)].

Pregnancy

Advise patients to notify their healthcare provider if they become pregnant or intend to become pregnant during TIGLUTIK therapy [see Use in Specific Populations (8.1)].

Lactation

Advise patients to notify their healthcare provider if they are breastfeeding or intend to breastfeed during TIGLUTIK therapy [see Use in Specific Populations (8.2)].

Manufactured for:
ITF Pharma, Inc.
850 Cassatt Road, Suite 350
Berwyn, PA 19312 USA

TIGLUTIK®is a licensed trademark of Italfarmaco SA
© 2020 ITF Pharma, Inc. All rights reserved.

PRINCIPAL DISPLAY PANEL - 300 mL Bottle Carton

NDC 70726-0303-1

Rxonly

Tiglutik®
riluzole
oral suspension
50 mg/10 mL (5 mg/mL)

For Oral Administration
Shake gently before use

Contents of this package:

- Two bottles, each containing 300 mL
- Two 10 mL oral syringes
- Two syringe bottle adapters
- Two syringe tip caps
- One Prescribing Information, including
  Instructions for Use

This product is a liquid suspension and is
supplied with syringes for oral administration.
Before use, please read the enclosed
Prescribing Information.

600 mL (two bottles/300 mL each)
Not To Be Dispensed Separately